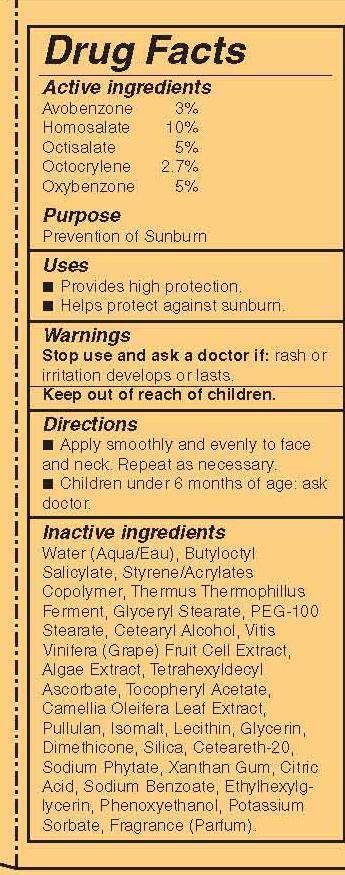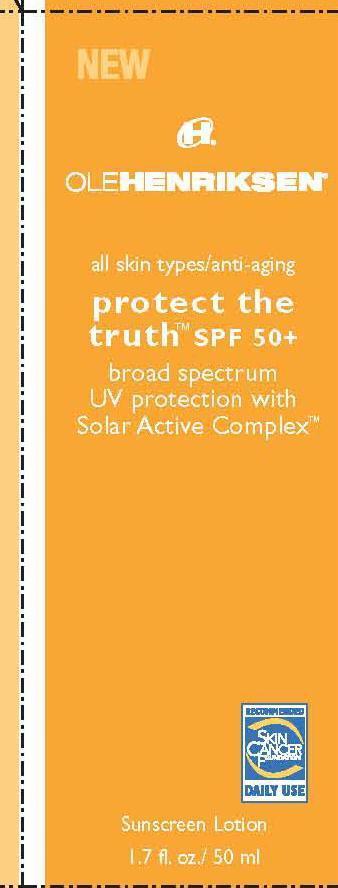 DRUG LABEL: Protect The Truth SPF 50
NDC: 51770-222 | Form: LOTION
Manufacturer: Ole Henriksen of Denmark
Category: otc | Type: HUMAN OTC DRUG LABEL
Date: 20130716

ACTIVE INGREDIENTS: AVOBENZONE 3 g/100 mL; HOMOSALATE 10 g/100 mL; OCTISALATE 5 g/100 mL; OCTOCRYLENE 2.7 g/100 mL; OXYBENZONE 5 g/100 mL
INACTIVE INGREDIENTS: BUTYLOCTYL SALICYLATE; GLYCERYL MONOSTEARATE; PEG-100 STEARATE; CETOSTEARYL ALCOHOL; TETRAHEXYLDECYL ASCORBATE; CAMELLIA OLEIFERA LEAF; PULLULAN; ISOMALT; GLYCERIN; DIMETHICONE; SILICON DIOXIDE; POLYOXYL 20 CETOSTEARYL ETHER; XANTHAN GUM; CITRIC ACID MONOHYDRATE; SODIUM BENZOATE; ETHYLHEXYLGLYCERIN; PHENOXYETHANOL; POTASSIUM SORBATE

Protect the Truth SPF 50

Active ingredients Purpose

Avobenzone 3% Prevention of Sunburn

Homosalate 10% Prevention of Sunburn

Octisalate 5% Prevention of Sunburn

Octocrylene 2.7% Prevention of Sunburn

Oxybenzone 5% Prevention of Sunburn

PURPOSE

prevention of sunburn

Keep out of reach of children

INDICATIONS AND USAGE

provides high protection

helps protect against sunburn

Stop use and ask a doctor if: rash or irritation develops or lasts.

DOSAGE AND ADMINISTRATION

apply smoothly and evenly to face and neck. repeat as necessary

children under 6 months of age: ask doctor

INACTIVE INGREDIENT

Water (Aqua/Eau), Butyloctyl Salicylate, Styrene/Acrylates Copolymer, Thermus Thermophillus Ferment, Glyceryl Stearate, PEG-100 Stearate, Cetearyl Alcohol, Vitis Vinifera (Grape) Fruit Cell Extract, Algae Extract, Tetrahexyldecyl Ascorbate, Tocopheryl Acetate, Camellia Oleifera Leaf Extract, Pullulan, Isomalt, Lecithin, Glycerin, Dimethicone, Silica, Ceteareth-20, Sodium Phytate, Xanthan Gum, Citric Acid, Sodium Benzoate, Ethylhexylglycerin, Phenoxyethanol, Potassium Sorbate, Fragrance (Parfum).

PACKAGE LABEL

OleHenriksen

all skin type/ Anti Aging

Protect the truth SPF 50+

broad spectrum UV Protection with Solar Active Complex

Sunscreen Lotion

1.7 fl.oz./ 50 ml